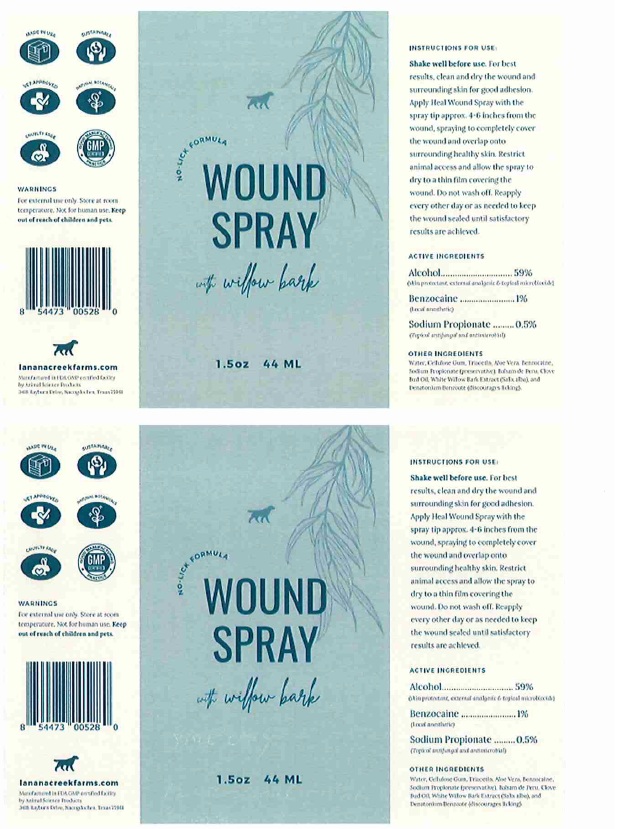 DRUG LABEL: Lanana Creek Farms Wound
NDC: 57932-006 | Form: LIQUID
Manufacturer: Animal Science Products, Inc.
Category: animal | Type: OTC ANIMAL DRUG LABEL
Date: 20250414

ACTIVE INGREDIENTS: ALCOHOL 59 g/100 mL; BENZOCAINE 1 g/100 mL; SODIUM PROPIONATE 0.5 g/100 mL
INACTIVE INGREDIENTS: WATER; CARBOXYMETHYLCELLULOSE SODIUM, UNSPECIFIED; TRIACETIN; ALOE VERA LEAF; BALSAM PERU; CLOVE OIL; SALIX ALBA BARK; DENATONIUM BENZOATE

Active Ingredient

Alcohol ..............59%
Benzocaine.........1%
Sodium Propionate........0.5%

Purpose

Provides soothing pain relief and antibacterial action for minor cuts and wounds on dogs.

Uses

Spray-on, no-lick liquid bandage for minor cuts and wounds on dogs.

Warnings

For external use only. Store at room temperature. Not for human use. Keep away from children and pets.

Directions

Shake well before use. For best results, clean and dry the wound and surrounding skin for good adhesion. Apply Heal Wound Spray with the spray tip approximately 4-6 inches from the wound, spraying to completely cover the wound and overlap onto surrounding healthy skin. Restrict animal access to allow the spray to dry to a thin film covering the wound. Do not wash off. Re-apply every other day or as needed to keep the wound sealed until satisfactory results are achieved.

Inactive Ingredients

Water, cellulose gum, triacetin, aloe vera, sodium propionate, balsam de peru, clove bud oil, White willow bark extract, denatonium benzoate.